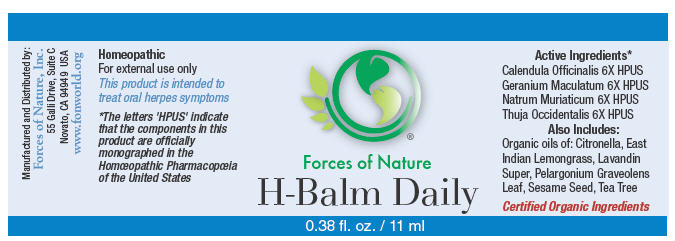 DRUG LABEL: H-Balm
NDC: 51393-6555 | Form: SOLUTION/ DROPS
Manufacturer: Forces of Nature
Category: homeopathic | Type: HUMAN OTC DRUG LABEL
Date: 20100824

ACTIVE INGREDIENTS: CALENDULA OFFICINALIS FLOWERING TOP 6 [hp_X]/1000 mL; Geranium Maculatum Root 6 [hp_X]/1000 mL; SODIUM CHLORIDE 6 [hp_X]/1000 mL; THUJA OCCIDENTALIS LEAFY TWIG 6 [hp_X]/1000 mL

H-Balm Daily

Drug Facts

Indications

For the treatment of oral herpes caused by herpes simplex 1 or 2 after diagnosis by a physician. Herpes is a contagious viral infection with symptoms of rashes or blisters, redness and pain.

ACTIVE INGREDIENT

PURPOSE

Homeopathic Active Ingredients [The letters 'HPUS' indicate that the components in this product are officially monographed in the Homœopathic Pharmacopœia of the United States.]
Equal part of: | Purpose
Calendula Officinalis 6X HPUS | Promotes healthy skin and healing
Geranium Maculatum 6X HPUS | Relief for skin ulcers
Natrum Muriaticum 6X HPUS | Relief for herpes, painful skin eruptions
Thuja Occidentalis 6X HPUS | Relief for herpes, skin eruptions, itching or burning pain

Also Contains Organic Oils of

Citronella, East Indian Lemongrass, Lavandin Super, Pelargonium Graveolens Leaf Oil, Sesame Seed, and Tea Tree.

Directions

Test area for skin sensitivity. Moisten cotton swab w water and allow 2-4 drops to fall on the cotton. Dab moistened swab to problem area twice daily as prophylactic (preventive) measure. Can also be applied directly from the bottle. Wash hands thoroughly after use. Avoid contact with eyes. Results improve consistently with use, so it is important to be consistent with this program. For best results, use with H-Balm.

Warnings

Viral infections are contagious, and this product will not prevent the spread of the virus that causes herpes or any other virus.

Some individuals may be sensitive to tea tree or other oils. Begin with a small drop to determine if the product causes any increased redness or irritation and discontinue use if it irritates your skin.

PREGNANCY OR BREAST FEEDING

If you are pregnant or breast-feeding, ask a health professional before use.

Keep out of the reach of children.

WHEN USING

If accidental ingestion of more than several drops, get medical help or contact a Poison Control Center.

STOP USE

For external use only. Avoid contact with eyes. Stop use and ask a doctor if condition worsens or symptoms last more than 7 days.

Manufactured by:
Forces of Nature, Inc.
55 Galli Drive, Suite C
Novato, CA 94949 USA
www.fonworld.org

Product questions?

877-975-3797

NDC#: 51393-6555-1 (11 ml) // 51393-6555-2 (33 ml)

Principal Display Panel - 11 ml Bottle Label

Forces of Nature

H-Balm Daily

0.38 fl. oz. / 11 ml